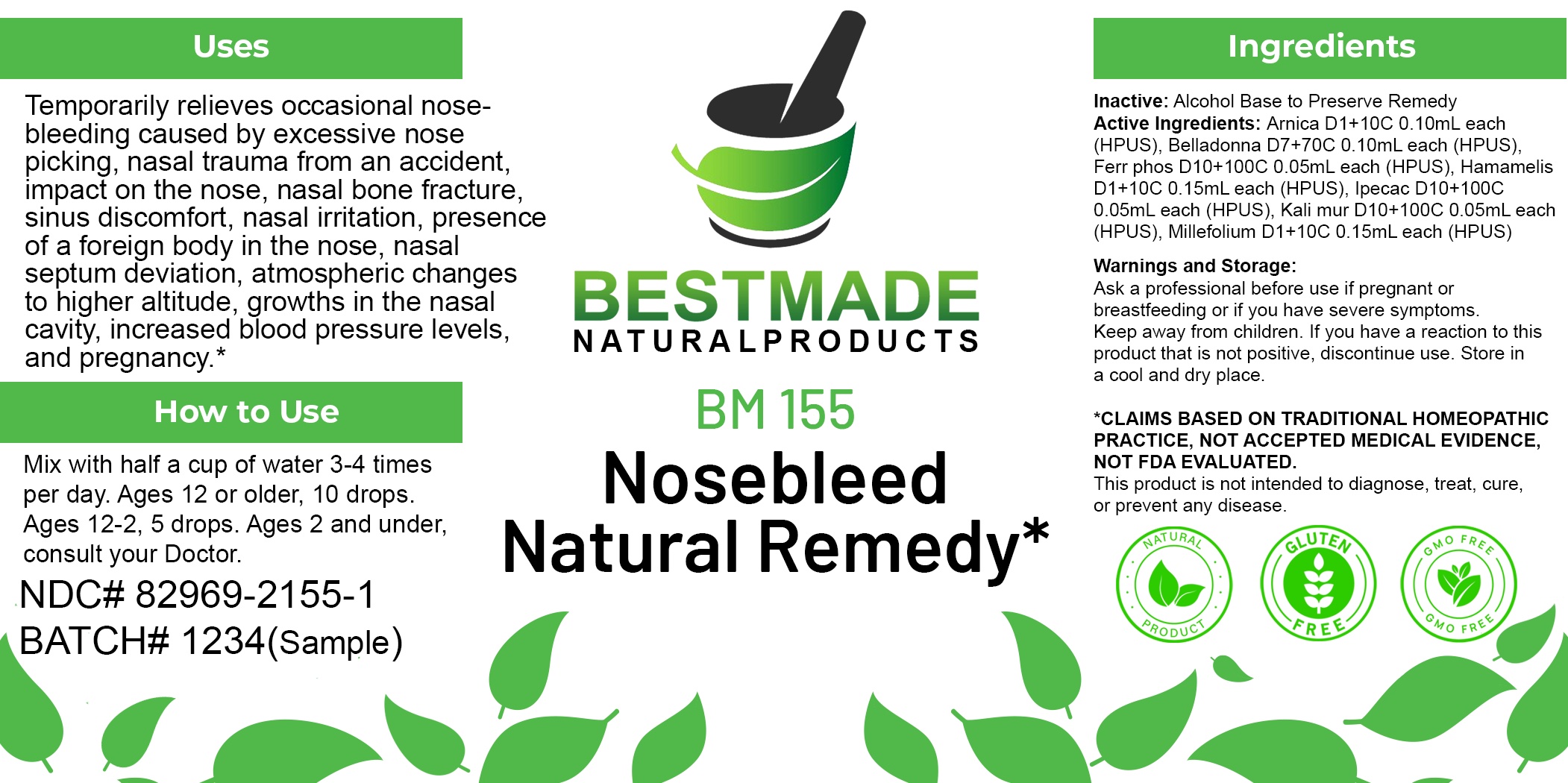 DRUG LABEL: Bestmade Natural Products BM155
NDC: 82969-2155 | Form: LIQUID
Manufacturer: Bestmade Natural Products
Category: homeopathic | Type: HUMAN OTC DRUG LABEL
Date: 20250218

ACTIVE INGREDIENTS: ARNICA MONTANA WHOLE 30 [hp_C]/30 [hp_C]; HAMAMELIS VIRGINIANA ROOT BARK/STEM BARK 30 [hp_C]/30 [hp_C]; FERROSOFERRIC PHOSPHATE 30 [hp_C]/30 [hp_C]; POTASSIUM CHLORIDE 30 [hp_C]/30 [hp_C]; ACHILLEA MILLEFOLIUM WHOLE 30 [hp_C]/30 [hp_C]; ATROPA BELLADONNA 30 [hp_C]/30 [hp_C]; IPECAC 30 [hp_C]/30 [hp_C]
INACTIVE INGREDIENTS: ALCOHOL 30 [hp_C]/30 [hp_C]

BM155

DOSAGE AND ADMINISTRATION

How to Use

Mix with half a cup of water 3-4 times per day. Ages 12 or older, 10 drops. Ages 12-2, 5 drops. Ages 2 and under, consult your Doctor.

Inactive:

Alcohol Base to Preserve Product

ACTIVE INGREDIENTS

Arnica D1+10C 0.10mL each (HPUS), Belladonna D7+70C 0.10mL each (HPUS), Ferr phos D10+100C 0.05mL each (HPUS), Hamamelis D1+10C 0.15mL each (HPUS), Ipecac D10+100C 0.05mL each (HPUS), Kali mur D10+100C 0.05mL each (HPUS), Millefolium D1+10C 0.15mL each (HPUS)

Uses

Temporarily relieves occasional nose-bleeding caused by excessive nose picking, nasal trauma from an accident, impact on the nose, nasal bone fracture, sinus discomfort, nasal irritation, presence of a foreign body in the nose, nasal septum deviation, atmospheric changes to higher altitude, growths in the nasal cavity, increased blood pressure levels, and pregnancy.*

Uses

Temporarily relieves occasional nose-bleeding caused by excessive nose picking, nasal trauma from an accident, impact on the nose, nasal bone fracture, sinus discomfort, nasal irritation, presence of a foreign body in the nose, nasal septum deviation, atmospheric changes to higher altitude, growths in the nasal cavity, increased blood pressure levels, and pregnancy.*

KEEP OUT OF REACH OF CHILDREN

Warnings and Storage:

Ask a professional before use if pregnant or breastfeeding or if you have severe symptoms.

Keep away from children. If you have a reaction to this product that is not positive, discontinue use. Store in a cool and dry place

*CLAIMS BASED ON TRADITIONAL HOMEOPATHIC PRACTICE, NOT ACCEPTED MEDICAL EVIDENCE NOT FDA EVALUATED.
This product is not intended to diagnose, treat, cure, or prevent any disease.

Warnings and Storage:

Ask a professional before use if pregnant or breastfeeding or if you have severe symptoms.

Keep away from children. If you have a reaction to this product that is not positive, discontinue use. Store in a cool and dry place

*CLAIMS BASED ON TRADITIONAL HOMEOPATHIC PRACTICE, NOT ACCEPTED MEDICAL EVIDENCE NOT FDA EVALUATED.
This product is not intended to diagnose, treat, cure, or prevent any disease.

Entire package label